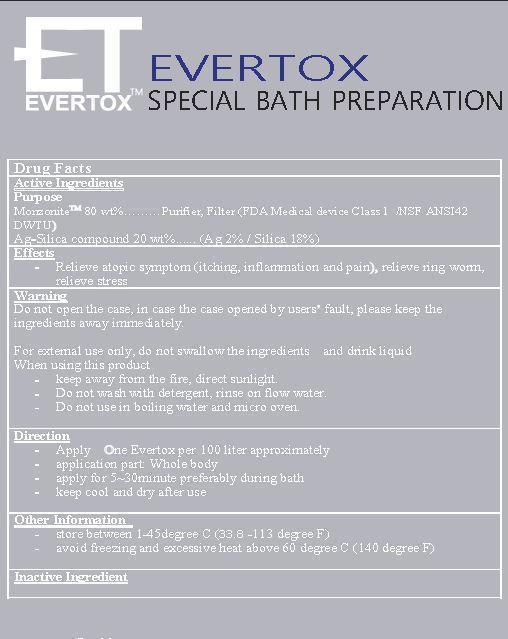 DRUG LABEL: EVERTOX SPECIAL BATH PREPARATIONS
NDC: 69474-1001 | Form: POWDER
Manufacturer: KMTR Co., Ltd.
Category: otc | Type: HUMAN OTC DRUG LABEL
Date: 20150111

ACTIVE INGREDIENTS: SILICON DIOXIDE 20 g/100 g
INACTIVE INGREDIENTS: SILVER; SODIUM ALUMINIUM SILICATE

Drug Facts

ACTIVE INGREDIENT

monzonite

INACTIVE INGREDIENT

silica compound

PURPOSE

relieve atopic symptom (itching, inflammation and pain), relieve ring worm, relieve stress

keep out of reach of the children

INDICATIONS AND USAGE

apply on evertox per 100 liter approximately
application part: whole body
apply for 5~30 minutes preferably during bath
keep cool and dry after use

WARNINGS

do not open the case, in case the case opened by user fault, please keep the ingredients away immediately

DOSAGE AND ADMINISTRATION

for external use only